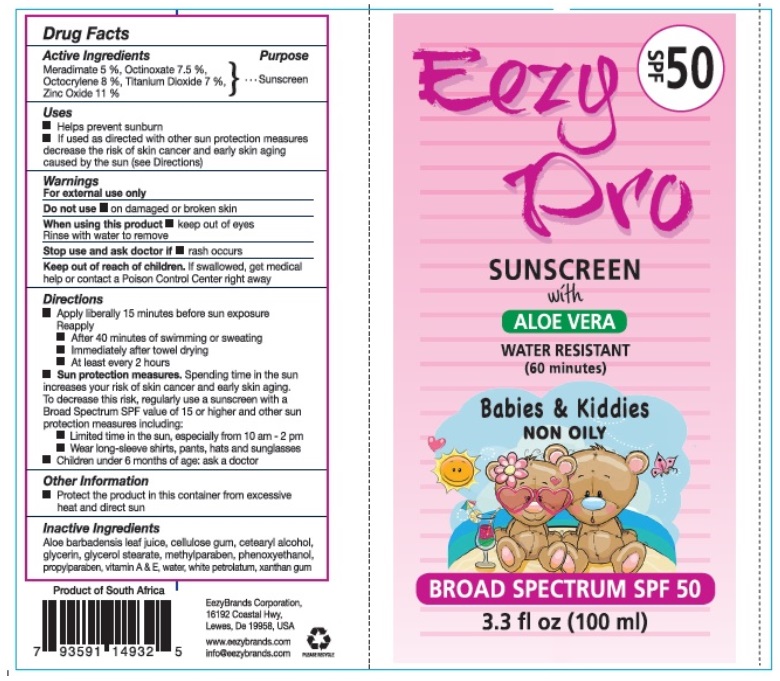 DRUG LABEL: Eezy Pro SPF 50
NDC: 70116-005 | Form: CREAM
Manufacturer: BIO EARTH MANUFACTURING (PTY) LTD
Category: otc | Type: HUMAN OTC DRUG LABEL
Date: 20241030

ACTIVE INGREDIENTS: MERADIMATE 5 g/100 mL; OCTINOXATE 7.5 g/100 mL; OCTOCRYLENE 8 g/100 mL; TITANIUM DIOXIDE 7 g/100 mL; ZINC OXIDE 11 g/100 mL
INACTIVE INGREDIENTS: BULBINE FRUTESCENS WHOLE; CARBOXYMETHYLCELLULOSE SODIUM, UNSPECIFIED FORM; CETOSTEARYL ALCOHOL; GLYCERIN; GLYCERYL MONOSTEARATE; METHYLPARABEN; PHENOXYETHANOL; PROPYLPARABEN; .ALPHA.-TOCOPHEROL; VITAMIN A; WATER; PETROLATUM; XANTHAN GUM

Eezy Pro

Actives

Meradimate, Octinoxate, Octocrylene, Titanium Dioxide, Zinc Oxide

Purpose

Sunsreen

Uses

- Helps prevent sunburn
- If used as directed with other sun protection measures decreases the risk of skin cancer and early skin aging caused by sun(see Directions)

Warnings

For external use only

Do not useon damaged or broken skin

When using this productkeep out of eyes. Rinse with water to remove.

Stop use and ask a doctorif rash occurs

Keep out of reach of children. If swallowed, get medical help or contact a Poison Control Center right away.

Directions

- Apply liberally 15 minutes before sun exposure

Reapply

- After 40 minutes of swimming or sweating
- Immediately after towel drying
- At least every 2 hours.

- Sun Protection Measures. Spending time in the sun increases your risk of skin cancer and early skin aging. To decrease this risk, regularly use a sunscreen with a Broad Spectrum SPF value of 15 or higher and other sun protection measures including:
- Limited time in the sun, espesially from 10 a.m - 2 p.m
- Wear long-sleeved shirts, pants, hats and sunglasses

- Children under 6 months of age: ask a doctor

Inactive ingredients

Aloe barbadensis leaf juice, Cellulose gum, Cetearyl alcohol, Glycerin, Glycerol Stearate, Methylparaben, Phenoxyethanol, Propylparaben,

Vitamin A & E, Water, White petrolatum, Xanthan gum

Other information

Protect the product in this container from excessive heat and direct sun